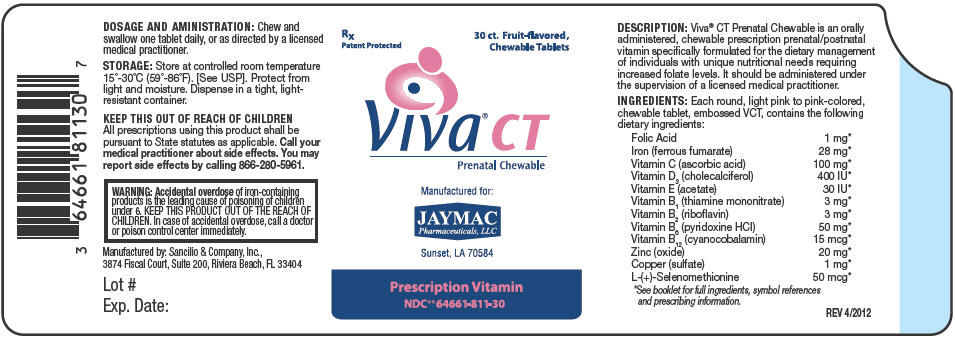 DRUG LABEL: Viva CT 
NDC: 64661-811 | Form: TABLET, CHEWABLE
Manufacturer: JayMac Pharmaceuticals LLC
Category: prescription | Type: HUMAN PRESCRIPTION DRUG LABEL
Date: 20120503

ACTIVE INGREDIENTS: FOLIC ACID 1 mg/1 1; FERROUS FUMARATE 28 mg/1 1; ASCORBIC ACID 100 mg/1 1; CHOLECALCIFEROL 400 [iU]/1 1; .ALPHA.-TOCOPHEROL ACETATE 30 [iU]/1 1; THIAMINE MONONITRATE 3 mg/1 1; RIBOFLAVIN 3 mg/1 1; PYRIDOXINE HYDROCHLORIDE 50 mg/1 1; CYANOCOBALAMIN 15 ug/1 1; ZINC OXIDE 20 mg/1 1; CUPRIC SULFATE ANHYDROUS 1 mg/1 1; Selenomethionine 50 ug/1 1
INACTIVE INGREDIENTS: XYLITOL; CELLULOSE, MICROCRYSTALLINE; POVIDONE; MAGNESIUM STEARATE; TALC; SUCRALOSE

Viva® CT Prenatal Chewable
IRON SUPPLEMENT

Rx Only

30ct round, light pink to pink-colored, fruit-flavored chewable tablets, embossed VCT

Prescription PRENATAL/POSTNATAL Vitamin

DESCRIPTION

Viva® CT Prenatal Chewable is an orally administered, chewable prescription PRENATAL/POSTNATAL vitamin specifically formulated for the dietary management of individuals with unique nutritional needs requiring increased folate levels. Viva® CT Prenatal Chewable should be administered under the supervision of a licensed medical practitioner.

Each ROUND, LIGHT TO PINK-colored, chewable tablet contains the following dietary ingredients:

Folic Acid | 1 mg [Daily Value not established for individuals with unique nutritional needs who are in need of nutritional supplementation as directed by a licensed medical practitioner.]
Iron (ferrous fumarate) | 28 mg
Vitamin C (ascorbic acid) | 100 mg
Vitamin D3 (cholecalciferol) | 400 IU
Vitamin E (acetate) | 30 IU
Vitamin B1 (thiamine mononitrate) | 3 mg
Vitamin B2 (riboflavin) | 3 mg
Vitamin B6 (pyridoxine HCl) | 50 mg
Vitamin B12 (cyanocobalamin) | 15 mcg
Zinc (oxide) | 20 mg
Copper (sulfate) | 1 mg
L-(+)-Selenomethionine [L-(+)-Selenomethionine as Selenium SeLECT® is a registered trademark of Sabinsa Corporation, Piscataway, NJ. It has CAS #3211-76-5, and is chemically known as the diasterioisomerically pure (S)-(+)-2-Amino-4(methylseleno)-butanoic acid.] | 50 mcg

Other Ingredients

Xylitol, Microcrystalline Cellulose, Povidone, Magnesium Stearate, Talc, Fruit Punch Flavor, Sucralose.

FOLATE REGULATION

The term "folate" are B vitamins that include folic acid and any forms of active pteroylglutamates regardless of the reduction state of the molecule. Folates, or vitamin B9, are primarily hydrolyzed in the intestinal jejunum and the liver to the active circulating form of folate, I-methylfolate, with an intermediate stable form, 5,10-methylenetetrahydrofolate. Folic acid, including the reduced forms [This product is a dietary supplement that - due to increased folate levels (AUG 3 1973 FR 20750), requires an Rx on the label because of increased risk associated with masking of vitamin B12 deficiency. As such, this product requires licensed medical supervision, an Rx status, and a National Drug Code (NDC) as required by pedigree reporting requirements.] such as folinic acid, may obscure pernicious anemia above 0.1 mg doses, and must be administered under the supervision of a licensed medical practitioner.

The 1971, 1972, 1973, 1980, 1984, 2000, and 2010 Federal Register Notices addressed this concern while establishing that increased folate was proper therapy in megaloblastic anemias - specifically where homocysteine levels were elevated or risk of neural tube defects (NTDs) was at issue. The Federal Register Notice of August 2, 1973 (38 FR 20750) specifically states that: Dietary supplement preparations are available without a prescription (21 CFR 121.1134). Levels higher than dietary supplement amounts are available only with a prescription. Folic acid - including reduced forms, may be added to medical foods as defined in section 5(b) (3) of the Orphan Drug Act (21 USC 360ee(b)(3)), or to food (21 CFR 172.345).

INDICATIONS AND USAGE

Viva® CT Prenatal Chewable is indicated for the distinct nutritional requirements of individuals in need of PRENATAL/POSTNATAL dietary supplementation as determined by a licensed medical practitioner. This product can be used fordietary management prior to conception. Viva® CT Prenatal Chewable should be administered under the supervision of a licensed medical practitioner.

CONTRAINDICATIONS

Viva® CT Prenatal Chewable is contraindicated in individuals with a known hypersensitivity to any of the ingredients.

WARNINGS

WARNING

Accidental overdose of iron-containing products is the leading cause of poisoning of children under 6. KEEP THIS PRODUCT OUT OF THE REACH OF CHILDREN. In case of accidental overdose, call a doctor or poison control center immediately.

PREGNANCY and NURSING MOTHERS

NURSING MOTHERS

Viva® CT Prenatal Chewable is intended for use as a PRENATAL/POSTNATAL vitamin for lactating and non-lactating mothers. Talk with your medical practitioner to ensure adequate prenatal/postnatal supplementation. Consult with your licensed medical practitioner before using Viva® CT Prenatal Chewable if pregnant or nursing.

PRECAUTIONS

Folate alone is improper therapy in the treatment of pernicious anemia and other megaloblastic anemias where vitamin B12 is deficient. Folate in doses above 0.1 mg daily may obscure pernicious anemia in that hematologic remission can occur while neurological manifestations progress.

PATIENT INFORMATION

Viva® CT Prenatal Chewable is a prescription PRENATAL/POSTNATAL vitamin to be used only under licensed medical supervision.

DRUG INTERACTIONS

Drugs which may interact with folate include:

- Antiepileptic drugs (AED): The AED class including, but not limited to, phenytoin, carbamazepine, primidone, valproic acid, fosphenytoin, valproate, phenobarbital and lamotrigine have been shown to impair folate absorption and increase the metabolism of circulating folate.
- Additionally, concurrent use of folic acid has been associated with enhanced phenytoin metabolism, lowering the level of the AED in the blood and allowing breakthrough seizures to occur. Caution should be used when prescribing this product among individuals who are receiving treatment with phenytoin and other anticonvulsants.
- Capecitabine: Folinic acid (5-formyltetrahydrofolate) may increase the toxicity of Capecitabine.
- Cholestyramine: Reduces folic acid absorption and reduces serum folate levels.
- Colestipol: Reduces folic acid absorption and reduces serum folate levels.
- Cycloserine: Reduces folic acid absorption and reduces serum folate levels.
- Dihydrofolate Reductase Inhibitors (DHFRI): DHFRIs block the conversion of folic acid to its active forms, and lower plasma and red blood cell folate levels. DHFRIs include aminopterin, methotrexate, pyrimethamine, triamterene, and trimethoprim.
- Fluoxetine: Fluoxetine exerts a noncompetitive inhibition of the 5-methyltetrahydrofolate active transport in the intestine.
- Isotretinoin: Reduced folate levels have occurred in some individuals taking isotretinoin.
- L-dopa, triamterene, colchicine, and trimethoprim may decrease plasma folate levels.
- Nonsteroidal Anti-inflammatory Drugs (NSAIDs): NSAIDs have been shown to inhibit some folate dependent enzymes in laboratory experiments.
- NSAIDs include ibuprofen, naproxen, indomethacin and sulindac.
- Oral Contraceptives: Serum folate levels may be depressed by oral contraceptive therapy.
- Methylprednisolone: Reduced serum folate levels have been noted after treatment with methylprednisolone.
- Pancreatic Enzymes: Reduced folate levels have occurred in some individuals taking pancreatic extracts, such as pancreatin and pancrelipase.
- Pentamidine: Reduced folate levels have been seen with prolonged intravenous pentamidine.
- Pyrimethamine: High levels of folic acid may result in decreased serum levels of pyrimethamine.
- Smoking and Alcohol: Reduced serum folate levels have been noted.
- Sulfasalazine: Inhibits the absorption and metabolism of folic acid.
- Metformin treatment in individuals with type 2 diabetes decreases serum folate.
- Warfarin can produce significant impairment in folate status after a 6-month therapy.
- Heme-iron: Can compete for transport and reduce folate absorption. Ensure adequate medical supervision to ensure proper iron levels.
- Folinic acid may enhance the toxicity of fluorouracil.
- Concurrent administration of chloramphenicol and folinic acid in folate-deficient patients may result in antagonism of the haematopoietic response to folate.
- Caution should be exercised with the concomitant use of folinic acid and trimethoprim-sulfamethoxazole for the acute treatment of Pneumocystis carinii pneumonia in patients with HIV infection as it is associated with increased rates of treatment failure and mortality in a placebo controlled study.

**Folate is a broad term that includes folic acid and all reduced forms including I-methylfolate and folinic acid. Viva® CT Prenatal Chewable does not contain I-methylfolate or folinic acid but these warnings are included as general folate information.

Drugs which interact with vitamin B6:

- Vitamin B6 should not be given to individuals receiving the drug levodopa because the action of levodopa is antagonized by vitamin B6. However, vitamin B6 may be used concurrently in individuals receiving a preparation containing both carbidopa and levodopa.

Drugs which may interact with vitamin B12:

- Antibiotics, cholestyramine, colchicines, colestipol, metformin, para-aminosalicylic acid, and potassium chloride may decrease the absorption of vitamin B12.
- Nitrous oxide can produce a functional vitamin B12 deficiency.

ADVERSE REACTIONS

Allergic sensitization has been reported following both oral and parenteral administration of folate. Paresthesia, somnolence, nausea, and headaches have been reported with vitamin B6. Mild transient diarrhea, polycythemia vera, itching, transitory exanthema and the feeling of swelling of the entire body have been associated with vitamin B12.

DOSAGE AND ADMINISTRATION

Chew and swallow one tablet daily, or as directed by a licensed medical practitioner.

STORAGE

Store at Controlled Room Temperature 15°- 30°C (59°- 86°F). [See USP]. Dispense in a tight, light-resistant container.

HOW SUPPLIED

Viva® CT Prenatal Chewable is supplied as round, light pink to pink-colored chewable tablets embossed VCT, and are dispensed in bottles of 30 tablets.

NDC 64661-811-30

Call your medical practitioner about side effects. You may report side effects by calling 866-280-5961.

KEEP THIS OUT OF REACH OF CHILDREN.

Rx Only

All prescriptions using this product shall be pursuant to State statutes as applicable.

Manufactured by: Sancilio & Company, Inc.,
3874 Fiscal Court, Suite 200, Riviera Beach, FL 33404

JAYMAC
Pharmaceuticals, LLC

MADE IN CHINA

REV 4/2012

PRINCIPAL DISPLAY PANEL - 30 Chewable Tablet Label

Rx
Patent Protected

30 ct. Fruit-flavored,
Chewable Tablets

Viva® CT
Prenatal Chewable

Manufactured for:
JAYMAC
Pharmaceuticals, LLC

Sunset, LA 70584

Prescription Vitamin
NDC^++64661-811-30